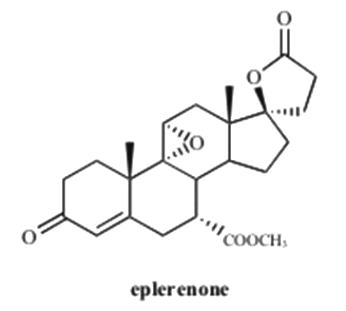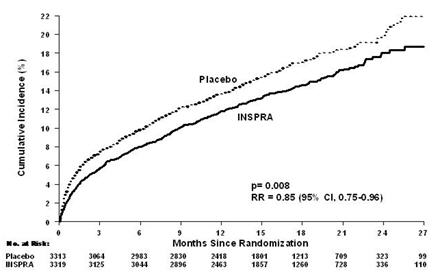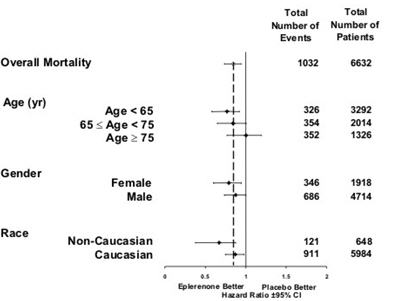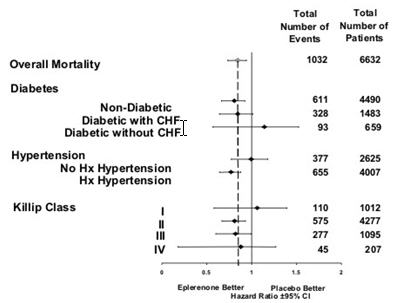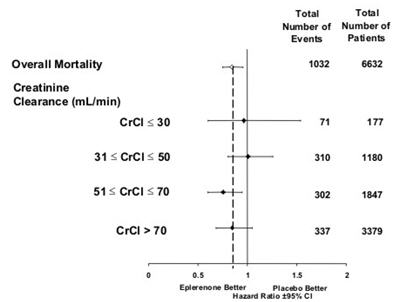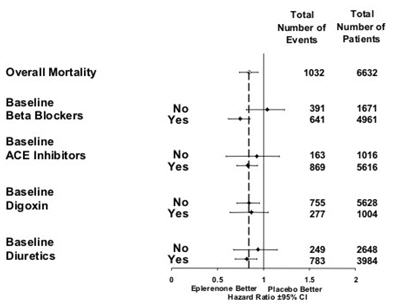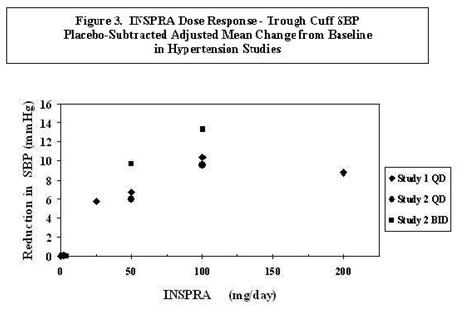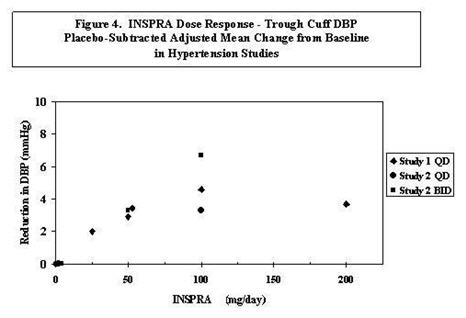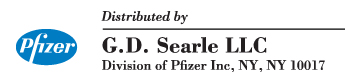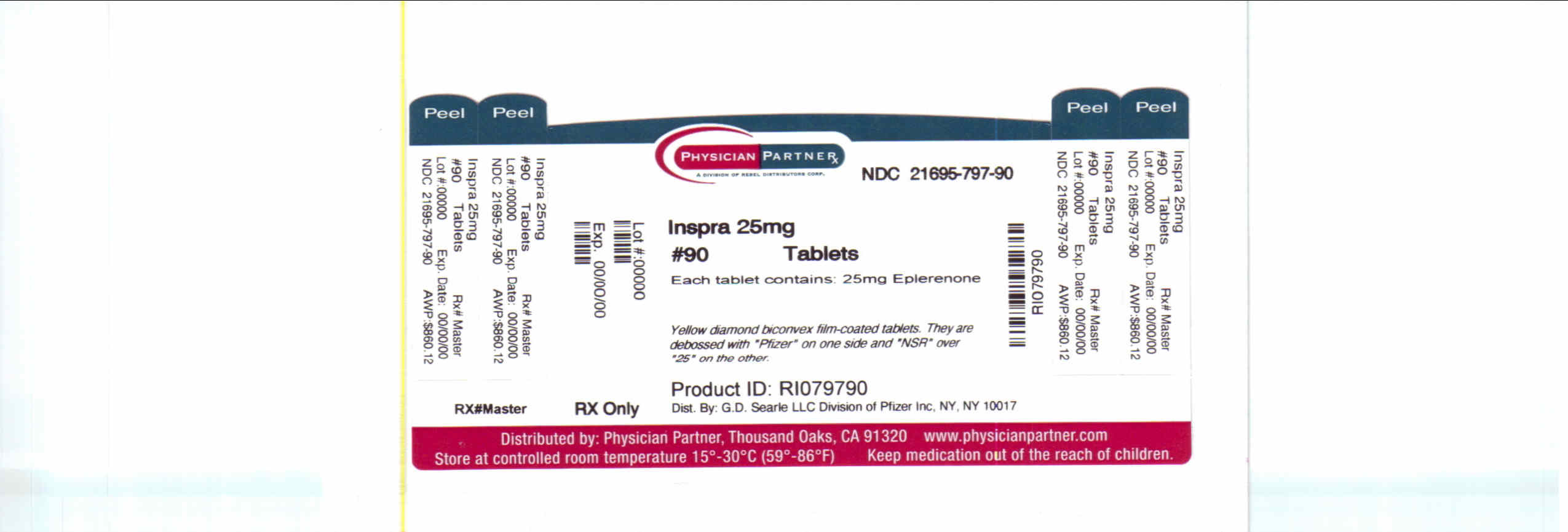 DRUG LABEL: Inspra
NDC: 21695-797 | Form: TABLET
Manufacturer: Rebel Distributors Corp
Category: prescription | Type: HUMAN PRESCRIPTION DRUG LABEL
Date: 20101228

ACTIVE INGREDIENTS: eplerenone 25 mg/1 1
INACTIVE INGREDIENTS: lactose; cellulose, microcrystalline; croscarmellose sodium; HYPROMELLOSES; sodium lauryl sulfate; talc; magnesium stearate; titanium dioxide; polyethylene glycol; polysorbate 80; ferric oxide yellow; ferric oxide red

HIGHLIGHTS OF PRESCRIBING INFORMATION

These highlights do not include all the information needed to use INSPRA safely and effectively. See full prescribing information for INSPRA.
INSPRA (eplerenone) tablet for oral use
Initial U.S. Approval: 2002

1 INDICATIONS AND USAGE

INSPRA is an aldosterone antagonist indicated for:

- Improving survival of stable patients with LV systolic dysfunction (LVEF ≤40%) and CHF after an acute myocardial infarction. (1.2)
- Hypertension, alone or combined with other agents. (1.3)

2 DOSAGE AND ADMINISTRATION

CHF Post-MI: Initiate treatment with 25 mg once daily. Titrate to maximum of 50 mg once daily within 4 weeks, as tolerated. Dose adjustments may be required based on potassium levels. (2.1)

Hypertension: 50 mg once daily, alone or combined with other antihypertensive agents. For inadequate response, increase to 50 mg twice daily. Higher dosages are not recommended. (2.2)

For all patients:

Measure serum potassium before starting INSPRA and periodically thereafter. (2.3)

3 DOSAGE FORMS AND STRENGTHS

Tablets: 25 mg, 50 mg (3)

4 CONTRAINDICATIONS

For all patients:

- Serum potassium >5.5 mEq/L at initiation (4)
- Creatinine clearance ≤30 mL/min (4)
- Concomitant use with strong CYP3A4 inhibitors (4, 7.1)

For the treatment of hypertension:

- Type 2 diabetes with microalbuminuria (4)
- Serum creatinine >2.0 mg/dL in males, >1.8 mg/dL in females (4)
- Creatinine clearance <50 mL/min (4)
- Concomitant use of potassium supplements or potassium-sparing diuretics (4)

5 WARNINGS AND PRECAUTIONS

- Hyperkalemia: Patients with decreased renal function and diabetics with proteinuria are at increased risk. Proper patient selection and monitoring and avoiding certain concomitant medications can minimize the risk. (5.1)

6 ADVERSE REACTIONS

CHF Post-MI: Most common adverse reactions (>2% and more frequent than with placebo): hyperkalemia and increased creatinine. (6.1)

Hypertension: Most common adverse reactions (≥2% and more frequent than with placebo): dizziness, diarrhea, coughing, fatigue and flu-like symptoms. (6.1)

To report SUSPECTED ADVERSE REACTIONS, contact Pfizer Inc. at 1-800-438-1985 or FDA at 1-800-FDA-1088 or www.fda.gov/medwatch

7 DRUG INTERACTIONS

- CYP3A4 Inhibitors: Reduce the starting dose for hypertension to 25 mg once daily when used with moderate CYP3A4 inhibitors (e.g., verapamil, erythromycin, saquinavir, fluconazole). (2.4, 7.1, 12.3)

FULL PRESCRIBING INFORMATION

1 INDICATIONS AND USAGE

1.1 Patient Selection Considerations

Serum potassium levels should be measured before initiating INSPRA therapy, and INSPRA should not be prescribed if serum potassium is >5.5 mEq/L. [See CONTRAINDICATIONS (4)].

1.2 Congestive Heart Failure Post-Myocardial Infarction

INSPRA is indicated to improve survival of stable patients with left ventricular (LV) systolic dysfunction (ejection fraction ≤40%) and clinical evidence of congestive heart failure (CHF) after an acute myocardial infarction (MI).

1.3 Hypertension

INSPRA is indicated for the treatment of hypertension. INSPRA may be used alone or in combination with other antihypertensive agents.

2 DOSAGE AND ADMINISTRATION

2.1 Congestive Heart Failure Post-Myocardial Infarction

Treatment should be initiated at 25 mg once daily and titrated to the recommended dose of 50 mg once daily, preferably within 4 weeks as tolerated by the patient. INSPRA may be administered with or without food.

Once treatment with INSPRA has begun, adjust the dose based on the serum potassium level as shown in Table 1.

Table 1. Dose Adjustment in Congestive Heart Failure Post-MI
Serum Potassium (mEq/L) | Action | Dose Adjustment
< 5.0 | Increase | 25 mg every other day to 25 mg once daily 25 mg once daily to 50 mg once daily
5.0–5.4 | Maintain | No adjustment
5.5–5.9 | Decrease | 50 mg once daily to 25 mg once daily 25 mg once daily to 25 mg every other day 25 mg every other day to withhold
≥ 6.0 | Withhold | Restart at 25 mg every other day when potassium levels fall to <5.5 mEq/L

2.2 Hypertension

The recommended starting dose of INSPRA is 50 mg administered once daily. The full therapeutic effect of INSPRA is apparent within 4 weeks. For patients with an inadequate blood pressure response to 50 mg once daily the dosage of INSPRA should be increased to 50 mg twice daily. Higher dosages of INSPRA are not recommended because they have no greater effect on blood pressure than 100 mg and are associated with an increased risk of hyperkalemia. [See CLINICAL STUDIES (14.2).]

2.3 Recommended Monitoring

Serum potassium should be measured before initiating INSPRA therapy, within the first week, and at one month after the start of treatment or dose adjustment. Serum potassium should be assessed periodically thereafter. Patient characteristics and serum potassium levels may indicate that additional monitoring is appropriate. [See WARNINGS AND PRECAUTIONS (5.1), ADVERSE REACTIONS (6.2).] In the EPHESUS study [See CLINICAL STUDIES (14.1)], the majority of hyperkalemia was observed within the first three months after randomization.

In all patients taking INSPRA who start taking a moderate CYP3A4 inhibitor, check serum potassium and serum creatinine in 3–7 days.

2.4 Dose Modifications for Specific Populations

For hypertensive patients receiving moderate CYP3A4 inhibitors (e.g., erythromycin, saquinavir, verapamil, and fluconazole), the starting dose of INSPRA should be reduced to 25 mg once daily. [See DRUG INTERACTIONS (7.1).]

No adjustment of the starting dose is recommended for the elderly or for patients with mild-to-moderate hepatic impairment. [See CLINICAL PHARMACOLOGY (12.3).]

3 DOSAGE FORMS AND STRENGTHS

- 25 mg tablets: yellow diamond biconvex film-coated tablets debossed with Pfizer on one side and NSR over 25 on the other
- 50 mg tablets: yellow diamond biconvex film-coated tablets debossed with Pfizer on one side and NSR over 50 on the other

4 CONTRAINDICATIONS

For All Patients

INSPRA is contraindicated in all patients with:

- serum potassium >5.5 mEq/L at initiation,
- creatinine clearance ≤30 mL/min, or
- concomitant administration of strong CYP3A4 inhibitors (e.g., ketoconazole, itraconazole, nefazodone, troleandomycin, clarithromycin, ritonavir, and nelfinavir). [See DRUG INTERACTIONS (7.1), CLINICAL PHARMACOLOGY (12.3).]

For Patients Treated for Hypertension

INSPRA is contraindicated for the treatment of hypertension in patients with:

- type 2 diabetes with microalbuminuria,
- serum creatinine >2.0 mg/dL in males or >1.8 mg/dL in females,
- creatinine clearance <50 mL/min, or
- concomitant administration of potassium supplements or potassium-sparing diuretics (e.g., amiloride, spironolactone, or triamterene). [See WARNINGS AND PRECAUTIONS (5.1), ADVERSE REACTIONS (6.2), DRUG INTERACTIONS (7), and CLINICAL PHARMACOLOGY (12.3).]

5 WARNINGS AND PRECAUTIONS

5.1 Hyperkalemia

Minimize the risk of hyperkalemia with proper patient selection and monitoring, and avoidance of certain concomitant medications [See CONTRAINDICATIONS (4), ADVERSE REACTIONS (6.2), and DRUG INTERACTIONS (7)]. Monitor patients for the development of hyperkalemia until the effect of INSPRA is established. Patients who develop hyperkalemia (>5.5 mEq/L) may continue INSPRA therapy with proper dose adjustment. Dose reduction decreases potassium levels. [See DOSAGE AND ADMINISTRATION (2.1).]

The rates of hyperkalemia increase with declining renal function. [See ADVERSE REACTIONS (6.2).] Patients with hypertension who have serum creatinine levels >2.0 mg/dL (males) or >1.8 mg/dL (females) or creatinine clearance ≤50 mL/min should not be treated with INSPRA. [See CONTRAINDICTIONS (4).] Patients with CHF post-MI who have serum creatinine levels >2.0 mg/dL (males) or >1.8 mg/dL (females) or creatinine clearance ≤50mL/min should be treated with INSPRA with caution.

Diabetic patients with CHF post-MI should also be treated with caution, especially those with proteinuria. The subset of patients in the EPHESUS study with both diabetes and proteinuria on the baseline urinalysis had increased rates of hyperkalemia compared to patients with either diabetes or proteinuria. [See ADVERSE REACTIONS (6.2).]

5.2 Impaired Hepatic Function

Mild-to-moderate hepatic impairment did not increase the incidence of hyperkalemia. In 16 subjects with mild-to-moderate hepatic impairment who received 400 mg of eplerenone, no elevations of serum potassium above 5.5 mEq/L were observed. The mean increase in serum potassium was 0.12 mEq/L in patients with hepatic impairment and 0.13 mEq/L in normal controls. The use of INSPRA in patients with severe hepatic impairment has not been evaluated. [See CLINICAL PHARMACOLOGY (12.3).]

5.3 Impaired Renal Function

Patients with decreased renal function are at increased risk of hyperkalemia. [See CONTRAINDICATIONS (4),WARNINGS AND PRECAUTIONS (5.1), ADVERSE REACTIONS (6.1).]

6 ADVERSE REACTIONS

The following adverse reactions are discussed in greater detail in other sections of the labeling:

- Hyperkalemia [See WARNINGS AND PRECAUTIONS (5.1)]

Because clinical trials are conducted under widely varying conditions, adverse reaction rates observed in the clinical trials of a drug cannot be directly compared to rates in clinical trials of another drug and may not reflect the rates observed in practice.

6.1 Clinical Trials Experience

Congestive Heart Failure Post-Myocardial Infarction

In EPHESUS, safety was evaluated in 3307 patients treated with INSPRA and 3301 placebo-treated patients. The overall incidence of adverse events reported with INSPRA (78.9%) was similar to placebo (79.5%). Adverse events occurred at a similar rate regardless of age, gender, or race. Patients discontinued treatment due to an adverse event at similar rates in either treatment group (4.4% INSPRA vs. 4.3% placebo), with the most common reasons for discontinuation being hyperkalemia, myocardial infarction, and abnormal renal function.

Adverse reactions that occurred more frequently in patients treated with INSPRA than placebo were hyperkalemia (3.4% vs. 2.0%) and increased creatinine (2.4% vs. 1.5%). Discontinuations due to hyperkalemia or abnormal renal function were less than 1.0% in both groups. Hypokalemia occurred less frequently in patients treated with INSPRA (0.6% vs. 1.6%).

The rates of sex hormone-related adverse events are shown in Table 2.

Table 2. Rates of Sex Hormone-Related Adverse Events in EPHESUS
 | Rates in Males |  |  | Rates in Females
 | Gynecomastia | Mastodynia | Either | Abnormal Vaginal Bleeding
INSPRA | 0.4% | 0.1% | 0.5% | 0.4%
Placebo | 0.5% | 0.1% | 0.6% | 0.4%

Hypertension

INSPRA has been evaluated for safety in 3091 patients treated for hypertension. A total of 690 patients were treated for over 6 months and 106 patients were treated for over 1 year.

In placebo-controlled studies, the overall rates of adverse events were 47% with INSPRA and 45% with placebo. Adverse events occurred at a similar rate regardless of age, gender, or race. Therapy was discontinued due to an adverse event in 3% of patients treated with INSPRA and 3% of patients given placebo. The most common reasons for discontinuation of INSPRA were headache, dizziness, angina pectoris/myocardial infarction, and increased GGT. The adverse events that were reported at a rate of at least 1% of patients and at a higher rate in patients treated with INSPRA in daily doses of 25 to 400 mg versus placebo are shown in Table 3.

Table 3. Rates (%) of Adverse Events Occurring in Placebo-Controlled Hypertension Studies in ≥1% of Patients Treated with INSPRA (25 to 400 mg) and at a More Frequent Rate than in Placebo-Treated Patients
 | INSPRA (n=945) | Placebo (n=372)
Metabolic
Hypercholesterolemia | 1 | 0
Hypertriglyceridemia | 1 | 0
Digestive
Diarrhea | 2 | 1
Abdominal pain | 1 | 0
Urinary
Albuminuria | 1 | 0
Respiratory
Coughing | 2 | 1
Central/Peripheral Nervous System
Dizziness | 3 | 2
Body as a Whole
Fatigue | 2 | 1
Influenza-like symptoms | 2 | 1
Note: Adverse events that are too general to be informative or are very common in the treated population are excluded.

Gynecomastia and abnormal vaginal bleeding were reported with INSPRA but not with placebo. The rates of these sex hormone-related adverse events are shown in Table 4. The rates increased slightly with increasing duration of therapy. In females, abnormal vaginal bleeding was also reported in 0.8% of patients on antihypertensive medications (other than spironolactone) in active control arms of the studies with INSPRA.

Table 4. Rates of Sex Hormone-Related Adverse Events with INSPRA in Hypertension Clinical Studies
 | Rates in Males |  |  | Rates in Females
 | Gynecomastia | Mastodynia | Either | Abnormal Vaginal Bleeding
All controlled studies | 0.5% | 0.8% | 1.0% | 0.6%
Controlled studies lasting ≥ 6 months | 0.7% | 1.3% | 1.6% | 0.8%
Open-label, long-term study | 1.0% | 0.3% | 1.0% | 2.1%

6.2 Clinical Laboratory Test Findings

Congestive Heart Failure Post-Myocardial Infarction

Creatinine: Increases of more than 0.5 mg/dL were reported for 6.5% of patients administered INSPRA and for 4.9% of placebo-treated patients.

Potassium: In EPHESUS [see CLINICAL STUDIES (14.1)], the frequencies of patients with changes in potassium (<3.5 mEq/L or >5.5 mEq/L or ≥6.0 mEq/L) receiving INSPRA compared with placebo are displayed in Table 5.

Table 5. Hypokalemia (<3.5 mEq/L) or Hyperkalemia (>5.5 or ≥6.0 mEq/L) in EPHESUS
Potassium (mEq/L) | INSPRA (N=3251) n (%) | Placebo (N=3237) n (%)
< 3.5 | 273 (8.4) | 424 (13.1)
>5.5 | 508 (15.6) | 363 (11.2)
≥ 6.0 | 180 (5.5) | 126 (3.9)

Table 6 shows the rates of hyperkalemia in EPHESUS as assessed by baseline renal function (creatinine clearance).

Table 6. Rates of Hyperkalemia (>5.5 mEq/L) in EPHESUS by Baseline Creatinine Clearance [Estimated using the Cockroft-Gault formula.]
Baseline Creatinine Clearance | INSPRA (N=508) n (%) | Placebo (N=363) n (%)
≤30 mL/min | 160 (32) | 82 (23)
31–50 mL/min | 122 (24) | 46 (13)
51–70 mL/min | 86 (17) | 48 (13)
>70 mL/min | 56 (11) | 32 (9)

Table 7 shows the rates of hyperkalemia in EPHESUS as assessed by two baseline characteristics: presence/absence of proteinuria from baseline urinalysis and presence/absence of diabetes. [See WARNINGS AND PRECAUTIONS (5.1).]

Table 7. Rates of Hyperkalemia (>5.5 mEq/L) in EPHESUS by Proteinuria and History of Diabetes [Diabetes assessed as positive medical history at baseline; proteinuria assessed by positive dipstick urinalysis at baseline.]
 | INSPRA (N=508) n (%) | Placebo (N=363) n (%)
Proteinuria, no Diabetes | 81 (16) | 40 (11)
Diabetes, no Proteinuria | 91 (18) | 47 (13)
Proteinuria and Diabetes | 132 (26) | 58 (16)

Hypertension

Potassium: In placebo-controlled fixed-dose studies, the mean increases in serum potassium were dose-related and are shown in Table 8 along with the frequencies of values >5.5 mEq/L.

Table 8. Increases in Serum Potassium in the Placebo-Controlled, Fixed-Dose Hypertension Studies of INSPRA
 |  | Mean Increase mEq/L | % >5.5 mEq/L
Daily Dosage | n
Placebo | 194 | 0 | 1
25 | 97 | 0.08 | 0
50 | 245 | 0.14 | 0
100 | 193 | 0.09 | 1
200 | 139 | 0.19 | 1
400 | 104 | 0.36 | 8.7

Patients with both type 2 diabetes and microalbuminuria are at increased risk of developing persistent hyperkalemia. In a study of such patients taking INSPRA 200 mg, the frequencies of maximum serum potassium levels >5.5 mEq/L were 33% with INSPRA given alone and 38% when INSPRA was given with enalapril.

Rates of hyperkalemia increased with decreasing renal function. In all studies, serum potassium elevations >5.5 mEq/L were observed in 10.4% of patients treated with INSPRA with baseline calculated creatinine clearance <70 mL/min, 5.6% of patients with baseline creatinine clearance of 70 to 100 mL/min, and 2.6% of patients with baseline creatinine clearance of >100 mL/min. [See WARNINGS AND PRECAUTIONS (5.1).]

Sodium: Serum sodium decreased in a dose-related manner. Mean decreases ranged from 0.7 mEq/L at 50 mg daily to 1.7 mEq/L at 400 mg daily. Decreases in sodium (<135 mEq/L) were reported for 2.3% of patients administered INSPRA and 0.6% of placebo-treated patients.

Triglycerides: Serum triglycerides increased in a dose-related manner. Mean increases ranged from 7.1 mg/dL at 50 mg daily to 26.6 mg/dL at 400 mg daily. Increases in triglycerides (above 252 mg/dL) were reported for 15% of patients administered INSPRA and 12% of placebo-treated patients.

Cholesterol: Serum cholesterol increased in a dose-related manner. Mean changes ranged from a decrease of 0.4 mg/dL at 50 mg daily to an increase of 11.6 mg/dL at 400 mg daily. Increases in serum cholesterol values greater than 200 mg/dL were reported for 0.3% of patients administered INSPRA and 0% of placebo-treated patients.

Liver Function Tests: Serum alanine aminotransferase (ALT) and gamma glutamyl transpeptidase (GGT) increased in a dose-related manner. Mean increases ranged from 0.8 U/L at 50 mg daily to 4.8 U/L at 400 mg daily for ALT and 3.1 U/L at 50 mg daily to 11.3 U/L at 400 mg daily for GGT. Increases in ALT levels greater than 120 U/L (3 times upper limit of normal) were reported for 15/2259 patients administered INSPRA and 1/351 placebo-treated patients. Increases in ALT levels greater than 200 U/L (5 times upper limit of normal) were reported for 5/2259 of patients administered INSPRA and 1/351 placebo-treated patients. Increases of ALT greater than 120 U/L and bilirubin greater than 1.2 mg/dL were reported 1/2259 patients administered INSPRA and 0/351 placebo-treated patients. Hepatic failure was not reported in patients receiving INSPRA.

BUN/Creatinine: Serum creatinine increased in a dose-related manner. Mean increases ranged from 0.01 mg/dL at 50 mg daily to 0.03 mg/dL at 400 mg daily. Increases in blood urea nitrogen to greater than 30 mg/dL and serum creatinine to greater than 2 mg/dL were reported for 0.5% and 0.2%, respectively, of patients administered INSPRA and 0% of placebo-treated patients.

Uric Acid: Increases in uric acid to greater than 9 mg/dL were reported in 0.3% of patients administered INSPRA and 0% of placebo-treated patients.

6.3 Postmarketing Experience

The following adverse reactions have been identified during postapproval use of INSPRA. Because these reactions are reported voluntarily from a population of uncertain size, it is not always possible to reliably estimate their frequency or establish a causal relationship to drug exposure.

Skin: angioneurotic edema, rash

7 DRUG INTERACTIONS

7.1 CYP3A4 Inhibitors

Because eplerenone metabolism is predominantly mediated via CYP3A4, do not use INSPRA with drugs that are strong inhibitors of CYP3A4. [See CONTRAINDICATIONS (4) and CLINICAL PHARMACOLOGY (12.3).]

In patients with hypertension taking moderate CYP3A4 inhibitors, reduce the starting dose of INSPRA to 25 mg once daily. [See DOSAGE AND ADMINISTRATION (2.3,2.4) and CLINICAL PHARMACOLOGY (12.3).]

7.2 ACE Inhibitors and Angiotensin II Receptor Antagonists

Congestive Heart Failure Post-Myocardial Infarction

In EPHESUS [see CLINICAL STUDIES (14.1)], 3020 (91%) patients receiving INSPRA 25 to 50 mg also received ACE inhibitors or angiotensin II receptor antagonists (ACEI/ARB). Rates of patients with maximum potassium levels >5.5 mEq/L were similar regardless of the use of ACEI/ARB.

Hypertension

In clinical studies of patients with hypertension, the addition of INSPRA 50 to 100 mg to ACE inhibitors and angiotensin II receptor antagonists increased mean serum potassium slightly (about 0.09–0.13 mEq/L). In a study in diabetics with microalbuminuria, INSPRA 200 mg combined with the ACE inhibitor enalapril 10 mg increased the frequency of hyperkalemia (serum potassium >5.5 mEq/L) from 17% on enalapril alone to 38%.

7.3 Lithium

A drug interaction study of eplerenone with lithium has not been conducted. Lithium toxicity has been reported in patients receiving lithium concomitantly with diuretics and ACE inhibitors. Serum lithium levels should be monitored frequently if INSPRA is administered concomitantly with lithium.

7.4 Nonsteroidal Anti-Inflammatory Drugs (NSAIDs)

A drug interaction study of eplerenone with an NSAID has not been conducted. The administration of other potassium-sparing antihypertensives with NSAIDs has been shown to reduce the antihypertensive effect in some patients and result in severe hyperkalemia in patients with impaired renal function. Therefore, when INSPRA and NSAIDs are used concomitantly, patients should be observed to determine whether the desired effect on blood pressure is obtained and monitored for changes in serum potassium levels.

8 USE IN SPECIFIC POPULATIONS

8.1 Pregnancy

Pregnancy Category B

There are no adequate and well-controlled studies in pregnant women. INSPRA should be used during pregnancy only if the potential benefit justifies the potential risk to the fetus.

Teratogenic Effects

Embryo-fetal development studies were conducted with doses up to 1000 mg/kg/day in rats and 300 mg/kg/day in rabbits (exposures up to 32 and 31 times the human AUC for the 100 mg/day therapeutic dose, respectively). No teratogenic effects were seen in rats or rabbits, although decreased body weight in maternal rabbits and increased rabbit fetal resorptions and post-implantation loss were observed at the highest administered dosage. Because animal reproduction studies are not always predictive of human response, INSPRA should be used during pregnancy only if clearly needed.

8.3 Nursing Mothers

The concentration of eplerenone in human breast milk after oral administration is unknown. However, preclinical data show that eplerenone and/or metabolites are present in rat breast milk (0.85:1 [milk:plasma] AUC ratio) obtained after a single oral dose. Peak concentrations in plasma and milk were obtained from 0.5 to 1 hour after dosing. Rat pups exposed by this route developed normally. Because many drugs are excreted in human milk and because of the unknown potential for adverse effects on the nursing infant, a decision should be made whether to discontinue nursing or discontinue the drug, taking into account the importance of the drug to the mother.

8.4 Pediatric Use

In a 10-week study of 304 hypertensive pediatric patients age 4 to 17 years treated with INSPRA up to 100 mg per day, doses that produced exposure similar to that in adults, INSPRA did not lower blood pressure effectively. In this study and in a 1-year pediatric safety study in 149 patients, the incidence of reported adverse events was similar to that of adults.

INSPRA has not been studied in hypertensive patients less than 4 years old because the study in older pediatric patients did not demonstrate effectiveness.

INSPRA has not been studied in pediatric patients with heart failure.

8.5 Geriatric Use

Congestive Heart Failure Post-Myocardial Infarction

Of the total number of patients in EPHESUS, 3340 (50%) were 65 and over, while 1326 (20%) were 75 and over. Patients greater than 75 years did not appear to benefit from the use of INSPRA. [See CLINICAL STUDIES (14.1).]

No differences in overall incidence of adverse events were observed between elderly and younger patients. However, due to age-related decreases in creatinine clearance, the incidence of laboratory-documented hyperkalemia was increased in patients 65 and older. [See WARNINGS AND PRECAUTIONS (5.1).]

Hypertension

Of the total number of subjects in clinical hypertension studies of INSPRA, 1123 (23%) were 65 and over, while 212 (4%) were 75 and over. No overall differences in safety or effectiveness were observed between elderly subjects and younger subjects.

10 OVERDOSAGE

No cases of human overdosage with eplerenone have been reported. Lethality was not observed in mice, rats, or dogs after single oral doses that provided Cmax exposures at least 25 times higher than in humans receiving eplerenone 100 mg/day. Dogs showed emesis, salivation, and tremors at a Cmax 41 times the human therapeutic Cmax, progressing to sedation and convulsions at higher exposures.

The most likely manifestation of human overdosage would be anticipated to be hypotension or hyperkalemia. Eplerenone cannot be removed by hemodialysis. Eplerenone has been shown to bind extensively to charcoal. If symptomatic hypotension should occur, supportive treatment should be instituted. If hyperkalemia develops, standard treatment should be initiated.

11 DESCRIPTION

INSPRA contains eplerenone, a blocker of aldosterone binding at the mineralocorticoid receptor.

Eplerenone is chemically described as Pregn-4-ene-7,21-dicarboxylic acid, 9,11-epoxy-17-hydroxy-3-oxo-, γ-lactone, methyl ester, (7α,11α,17α)-. Its empirical formula is C24H30O6 and it has a molecular weight of 414.50. The structural formula of eplerenone is represented below:

Eplerenone is an odorless, white to off-white crystalline powder. It is very slightly soluble in water, with its solubility essentially pH-independent. The octanol/water partition coefficient of eplerenone is approximately 7.1 at pH 7.0.

INSPRA for oral administration contains 25 mg or 50 mg of eplerenone and the following inactive ingredients: lactose, microcrystalline cellulose, croscarmellose sodium, hypromellose, sodium lauryl sulfate, talc, magnesium stearate, titanium dioxide, polyethylene glycol, polysorbate 80, and iron oxide yellow and iron oxide red.

12 CLINICAL PHARMACOLOGY

12.1 Mechanism of Action

Eplerenone binds to the mineralocorticoid receptor and blocks the binding of aldosterone, a component of the renin-angiotensin-aldosterone-system (RAAS). Aldosterone synthesis, which occurs primarily in the adrenal gland, is modulated by multiple factors, including angiotensin II and non-RAAS mediators such as adrenocorticotropic hormone (ACTH) and potassium. Aldosterone binds to mineralocorticoid receptors in both epithelial (e.g., kidney) and nonepithelial (e.g., heart, blood vessels, and brain) tissues and increases blood pressure through induction of sodium reabsorption and possibly other mechanisms.

Eplerenone has been shown to produce sustained increases in plasma renin and serum aldosterone, consistent with inhibition of the negative regulatory feedback of aldosterone on renin secretion. The resulting increased plasma renin activity and aldosterone circulating levels do not overcome the effects of eplerenone.

Eplerenone selectively binds to recombinant human mineralocorticoid receptors relative to its binding to recombinant human glucocorticoid, progesterone, and androgen receptors.

12.3 Pharmacokinetics

Eplerenone is cleared predominantly by cytochrome P450 (CYP) 3A4 metabolism, with an elimination half-life of 4 to 6 hours. Steady state is reached within 2 days. Absorption is not affected by food. Inhibitors of CYP3A4 (e.g., ketoconazole, saquinavir) increase blood levels of eplerenone.

Absorption and Distribution

Mean peak plasma concentrations of eplerenone are reached approximately 1.5 hours following oral administration. The absolute bioavailability of eplerenone is 69% following administration of a 100 mg oral tablet. Both peak plasma levels (Cmax) and area under the curve (AUC) are dose proportional for doses of 25 to 100 mg and less than proportional at doses above 100 mg.

The plasma protein binding of eplerenone is about 50% and it is primarily bound to alpha 1-acid glycoproteins. The apparent volume of distribution at steady state ranged from 43 to 90 L. Eplerenone does not preferentially bind to red blood cells.

Metabolism and Excretion

Eplerenone metabolism is primarily mediated via CYP3A4. No active metabolites of eplerenone have been identified in human plasma.

Less than 5% of an eplerenone dose is recovered as unchanged drug in the urine and feces. Following a single oral dose of radiolabeled drug, approximately 32% of the dose was excreted in the feces and approximately 67% was excreted in the urine. The elimination half-life of eplerenone is approximately 4 to 6 hours. The apparent plasma clearance is approximately 10 L/hr.

Age, Gender, and Race

The pharmacokinetics of eplerenone at a dose of 100 mg once daily has been investigated in the elderly (≥65 years), in males and females, and in Blacks. At steady state, elderly subjects had increases in Cmax (22%) and AUC (45%) compared with younger subjects (18 to 45 years). The pharmacokinetics of eplerenone did not differ significantly between males and females. At steady state, Cmax was 19% lower and AUC was 26% lower in Blacks. [See DOSAGE AND ADMINISTRATION (2.4) and USE IN SPECIFIC POPULATIONS (8.5).]

Renal Impairment

The pharmacokinetics of eplerenone was evaluated in patients with varying degrees of renal impairment and in patients undergoing hemodialysis. Compared with control subjects, steady state AUC and Cmax were increased by 38% and 24%, respectively, in patients with severe renal impairment and were decreased by 26% and 3%, respectively, in patients undergoing hemodialysis. No correlation was observed between plasma clearance of eplerenone and creatinine clearance. Eplerenone is not removed by hemodialysis. [See WARNINGS AND PRECAUTIONS (5.3).]

Hepatic Impairment

The pharmacokinetics of eplerenone 400 mg has been investigated in patients with moderate (Child-Pugh Class B) hepatic impairment and compared with normal subjects. Steady state Cmax and AUC of eplerenone were increased by 3.6% and 42%, respectively.

Heart Failure

The pharmacokinetics of eplerenone 50 mg was evaluated in 8 patients with heart failure (NYHA classification II–IV) and 8 matched (gender, age, weight) healthy controls. Compared with the controls, steady state AUC and Cmax in patients with stable heart failure were 38% and 30% higher, respectively.

Drug-Drug Interactions [See DRUG INTERACTIONS (7).]

Eplerenone is metabolized primarily by CYP3A4. Inhibitors of CYP3A4 cause increased exposure [see DRUG INTERACTIONS (7.1)].

Drug-drug interaction studies were conducted with a 100 mg dose of eplerenone.

A pharmacokinetic study evaluating the administration of a single dose of INSPRA 100 mg with ketoconazole 200 mg two times a day, a strong inhibitor of the CYP3A4 pathway, showed a 1.7-fold increase in Cmax of eplerenone and a 5.4-fold increase in AUC of eplerenone.

Administration of eplerenone with moderate CYP3A4 inhibitors (e.g., erythromycin 500 mg BID, verapamil 240 mg once daily, saquinavir 1200 mg three times a day, fluconazole 200 mg once daily) resulted in increases in Cmax of eplerenone ranging from 1.4- to 1.6-fold and AUC from 2.0- to 2.9-fold.

Grapefruit juice caused only a small increase (about 25%) in exposure.

Eplerenone is not an inhibitor of CYP1A2, CYP3A4, CYP2C19, CYP2C9, or CYP2D6. Eplerenone did not inhibit the metabolism of amiodarone, amlodipine, astemizole, chlorzoxazone, cisapride, dexamethasone, dextromethorphan, diclofenac, 17α-ethinyl estradiol, fluoxetine, losartan, lovastatin, mephobarbital, methylphenidate, methylprednisolone, metoprolol, midazolam, nifedipine, phenacetin, phenytoin, simvastatin, tolbutamide, triazolam, verapamil, and warfarin in vitro. Eplerenone is not a substrate or an inhibitor of P-Glycoprotein at clinically relevant doses.

No clinically significant drug-drug pharmacokinetic interactions were observed when eplerenone was administered with cisapride, cyclosporine, digoxin, glyburide, midazolam, oral contraceptives (norethindrone/ethinyl estradiol), simvastatin, or warfarin. St. John's Wort (a CYP3A4 inducer) caused a small (about 30%) decrease in eplerenone AUC.

No significant changes in eplerenone pharmacokinetics were observed when eplerenone was administered with aluminum- and magnesium-containing antacids.

13 NONCLINICAL TOXICOLOGY

13.1 Carcinogenesis, Mutagenesis, Impairment of Fertility

Eplerenone was non-genotoxic in a battery of assays including in vitro bacterial mutagenesis (Ames test in Salmonella spp. and E. Coli), in vitro mammalian cell mutagenesis (mouse lymphoma cells), in vitro chromosomal aberration (Chinese hamster ovary cells), in vivo rat bone marrow micronucleus formation, and in vivo/ex vivo unscheduled DNA synthesis in rat liver.

There was no drug-related tumor response in heterozygous P53 deficient mice when tested for 6 months at dosages up to 1000 mg/kg/day (systemic AUC exposures up to 9 times the exposure in humans receiving the 100 mg/day therapeutic dose). Statistically significant increases in benign thyroid tumors were observed after 2 years in both male and female rats when administered eplerenone 250 mg/kg/day (highest dose tested) and in male rats only at 75 mg/kg/day. These dosages provided systemic AUC exposures approximately 2 to 12 times higher than the average human therapeutic exposure at 100 mg/day. Repeat dose administration of eplerenone to rats increases the hepatic conjugation and clearance of thyroxin, which results in increased levels of TSH by a compensatory mechanism. Drugs that have produced thyroid tumors by this rodent-specific mechanism have not shown a similar effect in humans.

Male rats treated with eplerenone at 1000 mg/kg/day for 10 weeks (AUC 17 times that at the 100 mg/day human therapeutic dose) had decreased weights of seminal vesicles and epididymides and slightly decreased fertility. Dogs administered eplerenone at dosages of 15 mg/kg/day and higher (AUC 5 times that at the 100 mg/day human therapeutic dose) had dose-related prostate atrophy. The prostate atrophy was reversible after daily treatment for 1 year at 100 mg/kg/day. Dogs with prostate atrophy showed no decline in libido, sexual performance, or semen quality. Testicular weight and histology were not affected by eplerenone in any test animal species at any dosage.

14 CLINICAL STUDIES

14.1 Congestive Heart Failure Post-Myocardial Infarction

The eplerenone post-acute myocardial infarction heart failure efficacy and survival study (EPHESUS) was a multinational, multicenter, double-blind, randomized, placebo-controlled study in patients clinically stable 3–14 days after an acute myocardial infarction (MI) with left ventricular dysfunction (as measured by left ventricular ejection fraction [LVEF] ≤40%) and either diabetes or clinical evidence of congestive heart failure (CHF) (pulmonary congestion by exam or chest x-ray or S3). Patients with CHF of valvular or congenital etiology, patients with unstable post-infarct angina, and patients with serum potassium >5.0 mEq/L or serum creatinine >2.5 mg/dL were to be excluded. Patients were allowed to receive standard post-MI drug therapy and to undergo revascularization by angioplasty or coronary artery bypass graft surgery.

Patients randomized to INSPRA were given an initial dose of 25 mg once daily and titrated to the target dose of 50 mg once daily after 4 weeks if serum potassium was < 5.0 mEq/L. Dosage was reduced or suspended anytime during the study if serum potassium levels were ≥ 5.5 mEq/L. [See DOSAGE AND ADMINISTRATION (2.1).]

EPHESUS randomized 6,632 patients (9.3% U.S.) at 671 centers in 27 countries. The study population was primarily white (90%, with 1% Black, 1% Asian, 6% Hispanic, 2% other) and male (71%). The mean age was 64 years (range, 22–94 years). The majority of patients had pulmonary congestion (75%) by exam or x-ray and were Killip Class II (64%). The mean ejection fraction was 33%. The average time to enrollment was 7 days post-MI. Medical histories prior to the index MI included hypertension (60%), coronary artery disease (62%), dyslipidemia (48%), angina (41%), type 2 diabetes (30%), previous MI (27%), and CHF (15%).

The mean dose of INSPRA was 43 mg/day. Patients also received standard care including aspirin (92%), ACE inhibitors (90%), ß-blockers (83%), nitrates (72%), loop diuretics (66%), or HMG-CoA reductase inhibitors (60%).

Patients were followed for an average of 16 months (range, 0–33 months). The ascertainment rate for vital status was 99.7%.

The co-primary endpoints for EPHESUS were (1) the time to death from any cause, and (2) the time to first occurrence of either cardiovascular (CV) mortality [defined as sudden cardiac death or death due to progression of congestive heart failure (CHF), stroke, or other CV causes] or CV hospitalization (defined as hospitalization for progression of CHF, ventricular arrhythmias, acute myocardial infarction, or stroke).

For the co-primary endpoint for death from any cause, there were 478 deaths in the INSPRA group (14.4%) and 554 deaths in the placebo group (16.7%). The risk of death with INSPRA was reduced by 15% [hazard ratio equal to 0.85 (95% confidence interval 0.75 to 0.96; p = 0.008 by log rank test)]. Kaplan-Meier estimates of all-cause mortality are shown in Figure 1 and the components of mortality are provided in Table 9.

Figure 1. Kaplan-Meier Estimates of All-Cause Mortality

Table 9. Components of All-Cause Mortality in EPHESUS
 | INSPRA (N=3319) n (%) | Placebo (N=3313) n (%) | Hazard Ratio | p-value
Death from any cause | 478 (14.4) | 554 (16.7) | 0.85 | 0.008
CV Death | 407 (12.3) | 483 (14.6) | 0.83 | 0.005
Non-CV Death | 60 (1.8) | 54 (1.6)
Unknown or unwitnessed death | 11 (0.3) | 17 (0.5)

Most CV deaths were attributed to sudden death, acute MI, and CHF.

The time to first event for the co-primary endpoint of CV death or hospitalization, as defined above, was longer in the INSPRA group (hazard ratio 0.87, 95% confidence interval 0.79 to 0.95, p = 0.002). An analysis that included the time to first occurrence of CV mortality and all CV hospitalizations (atrial arrhythmia, angina, CV procedures, progression of CHF, MI, stroke, ventricular arrhythmia, or other CV causes) showed a smaller effect with a hazard ratio of 0.92 (95% confidence interval 0.86 to 0.99; p = 0.028). The combined endpoints, including combined all-cause hospitalization and mortality were driven primarily by CV mortality. The combined endpoints in EPHESUS, including all-cause hospitalization and all-cause mortality, are presented in Table 10.

Table 10. Rates of Death or Hospitalization in EPHESUS
Event | INSPRA n (%) | Placebo n (%)
CV death or hospitalization for progression of CHF, stroke, MI or ventricular arrhythmia [Co-Primary Endpoint.] | 885 (26.7) | 993 (30.0)
Death | 407 (12.3) | 483 (14.6)
Hospitalization | 606 (18.3) | 649 (19.6)
CV death or hospitalization for progression of CHF, stroke, MI, ventricular arrhythmia, atrial arrhythmia, angina, CV procedures, or other CV causes (PVD; Hypotension) | 1516 (45.7) | 1610 (48.6)
Death | 407 (12.3) | 483 (14.6)
Hospitalization | 1281 (38.6) | 1307 (39.5)
All-cause death or hospitalization | 1734 (52.2) | 1833 (55.3)
Death | 478 (14.4) | 554 (16.7)
Hospitalization | 1497 (45.1) | 1530 (46.2)

Mortality hazard ratios varied for some subgroups as shown in Figure 2. Mortality hazard ratios appeared favorable for INSPRA for both genders and for all races or ethnic groups, although the numbers of non-Caucasians were low (648, 10%). Patients with diabetes without clinical evidence of CHF and patients greater than 75 years did not appear to benefit from the use of INSPRA. Such subgroup analyses must be interpreted cautiously.

Analyses conducted for a variety of CV biomarkers did not confirm a mechanism of action by which mortality was reduced.

14.2 Hypertension

The safety and efficacy of INSPRA have been evaluated alone and in combination with other antihypertensive agents in clinical studies of 3091 hypertensive patients. The studies included 46% women, 14% Blacks, and 22% elderly (age ≥65). The studies excluded patients with elevated baseline serum potassium (>5.0 mEq/L) and elevated baseline serum creatinine (generally >1.5 mg/dL in males and >1.3 mg/dL in females).

Two fixed-dose, placebo-controlled, 8- to 12-week monotherapy studies in patients with baseline diastolic blood pressures of 95 to 114 mm Hg were conducted to assess the antihypertensive effect of INSPRA. In these two studies, 611 patients were randomized to INSPRA and 140 patients to placebo. Patients received INSPRA in doses of 25 to 400 mg daily as either a single daily dose or divided into two daily doses. The mean placebo-subtracted reductions in trough cuff blood pressure achieved by INSPRA in these studies at doses up to 200 mg are shown in Figures 3 and 4.

Patients treated with INSPRA 50 to 200 mg daily experienced significant decreases in sitting systolic and diastolic blood pressure at trough with differences from placebo of 6–13 mm Hg (systolic) and 3–7 mm Hg (diastolic). These effects were confirmed by assessments with 24-hour ambulatory blood pressure monitoring (ABPM). In these studies, assessments of 24-hour ABPM data demonstrated that INSPRA, administered once or twice daily, maintained antihypertensive efficacy over the entire dosing interval. However, at a total daily dose of 100 mg, INSPRA administered as 50 mg twice per day produced greater trough cuff (4/3 mm Hg) and ABPM (2/1 mm Hg) blood pressure reductions than 100 mg given once daily.

Blood pressure lowering was apparent within 2 weeks from the start of therapy with INSPRA, with maximal antihypertensive effects achieved within 4 weeks. Stopping INSPRA following treatment for 8 to 24 weeks in six studies did not lead to adverse event rates in the week following withdrawal of INSPRA greater than following placebo or active control withdrawal. Blood pressures in patients not taking other antihypertensives rose 1 week after withdrawal of INSPRA by about 6/3 mm Hg, suggesting that the antihypertensive effect of INSPRA was maintained through 8 to 24 weeks.

Blood pressure reductions with INSPRA in the two fixed-dose monotherapy studies and other studies using titrated doses, as well as concomitant treatments, were not significantly different when analyzed by age, gender, or race with one exception. In a study in patients with low renin hypertension, blood pressure reductions in Blacks were smaller than those in whites during the initial titration period with INSPRA.

INSPRA has been studied concomitantly with treatment with ACE inhibitors, angiotensin II receptor antagonists, calcium channel blockers, beta blockers, and hydrochlorothiazide. When administered concomitantly with one of these drugs INSPRA usually produced its expected antihypertensive effects.

There was no significant change in average heart rate among patients treated with INSPRA in the combined clinical studies. No consistent effects of INSPRA on heart rate, QRS duration, or PR or QT interval were observed in 147 normal subjects evaluated for electrocardiographic changes during pharmacokinetic studies.

16 HOW SUPPLIED/STORAGE AND HANDLING

INSPRA Tablets, 25 mg, are yellow diamond biconvex film-coated tablets. They are debossed with Pfizer on one side and NSR over 25 on the other. They are supplied as follows:

NDC Number | Size
21695-797-90 | Bottle of 90 tablets

STORAGE AND HANDLING

Store at 25°C (77°F); excursions permitted to 15–30°C (59–86°F) [See USP Controlled Room Temperature].

17 PATIENT COUNSELING INFORMATION

Patients receiving INSPRA should be informed:

- Not to use strong CYP3A4 inhibitors, such as ketoconazole, clarithromycin, nefazodone, ritonavir, and nelfinavir.
- Not to use potassium supplements or salt substitutes containing potassium without consulting the prescribing physician.
- To call their physician if they experience dizziness, diarrhea, vomiting, rapid or irregular heartbeat, lower extremity edema, or difficulty breathing.
- That periodic monitoring of blood pressure and serum potassium is important.

[See CONTRAINDICATIONS (4); WARNINGS AND PRECAUTIONS (5.1); and DRUG INTERACTIONS (7).]

LAB-0079-12

Repackaged by:

Rebel Distributors Corp

Thousand Oaks, CA 91320